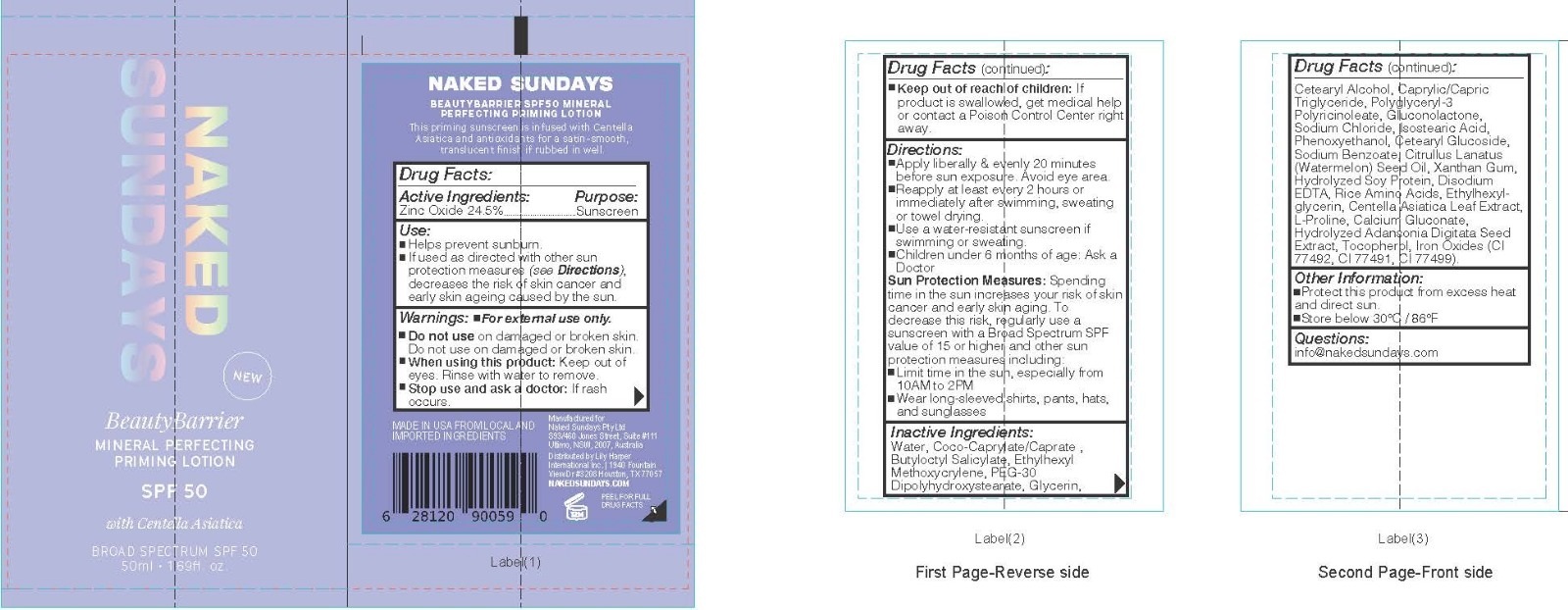 DRUG LABEL: BeautyBarrier
NDC: 81104-282 | Form: LOTION
Manufacturer: NAKED SUNDAYS PTY LTD
Category: otc | Type: HUMAN OTC DRUG LABEL
Date: 20260115

ACTIVE INGREDIENTS: ZINC OXIDE 24.5 g/100 mL
INACTIVE INGREDIENTS: PROLINE; POLYGLYCERYL-3 PENTARICINOLEATE; GLUCONOLACTONE; RICE AMINO ACIDS; ETHYLHEXYL METHOXYCRYLENE; WATER; CITRULLUS LANATUS (WATERMELON) SEED OIL; HYDROLYZED SOY PROTEIN (ENZYMATIC; 2000 MW); ISOSTEARIC ACID; GLYCERIN; CENTELLA ASIATICA LEAF; SODIUM BENZOATE; ETHYLHEXYLGLYCERIN; ADANSONIA DIGITATA SEED; SODIUM CHLORIDE; CETEARYL GLUCOSIDE; XANTHAN GUM; CALCIUM GLUCONATE; CI 77492; CI 77491; CI 77499; TOCOPHEROL; CETEARYL ALCOHOL; EDETATE DISODIUM; COCO-CAPRYLATE/CAPRATE; CAPRYLIC/CAPRIC TRIGLYCERIDE; PHENOXYETHANOL; PEG-30 DIPOLYHYDROXYSTEARATE (5000 MW); BUTYLOCTYL SALICYLATE

BeautyBarrier

Active Ingredients

Zinc Oxide 24.5%.

Purpose

Sunscreen

Inactive Ingredients

Butyloctyl Salicylate, Calcium Gluconate, Caprylic/CapricTriglyceride, Centella Asiatica Leaf Extract, Cetearyl Alcohol, Cetearyl Glucoside, Citrullus Lanatus (Watermelon) Seed Oil, Coco-Caprylate/Caprate, Disodium EDTA, Ethylhexyl Methoxycrylene, Ethylhexylglycerin, Gluconolactone, Glycerin, Hydrolyzed Adansonia Digitata Seed Extract, Hydrolyzed Soy Protein, Iron Oxides (CI 77492, CI 77491, CI 77499), Isostearic Acid, L-Proline, PEG-30 Dipolyhydroxystearate, Phenoxyethanol, Polyglyceryl-3 Polyricinoleate, Rice Amino Acids, Sodium Benzoate, Sodium Chloride, Tocopherol, Water, Xanthan Gum

Other Information

Protect this product from excess heat
and direct sun.

Store below 30°C / 86°F

Questions:
info@nakedsundays.com

usage

Helps prevent sunburn.

If used as directed with other sun protection measures (see Directions), decreases the risk of skin cancer and
early skin ageing caused by the sun.

Warning

Warnings: For external use only.

Do not use on damaged or broken skin.

When using this product: Keep out of eyes. Rinse with water to remove.

Stop use and ask a doctor: If rash occurs.

Dosage

Directions:
Apply liberally & evenly 15 minutes before sun exposure. Avoid eye area.

Reapply at least every 2 hours or immediately after swimming, sweating
or towel drying.

Use a water-resistant sunscreen if swimming or sweating.

Children under 6 months of age: Ask a Doctor

Other Safety Information

Sun Protection Measures: Spending time in the sun increases your risk of skin cancer and early skin aging. To decrease this risk, regularly use a sunscreen with a Broad Spectrum SPF value of 15 or higher and other sun protection measures including:

Limit time in the sun, especially from 10AM to 2PM

Wear long-sleeved shirts, pants, hats, and sunglasses

Keep out of reach of children: If product is swallowed, get medical help or contact a Poison Control Center right away.

Label

BeautyBarrier

MINERAL PERFECTING PRIMING LOTION

SPF50

with Centella Asiatica

BROAD SPECTRUM SPF 50

50ml • 1.69fl. oz.